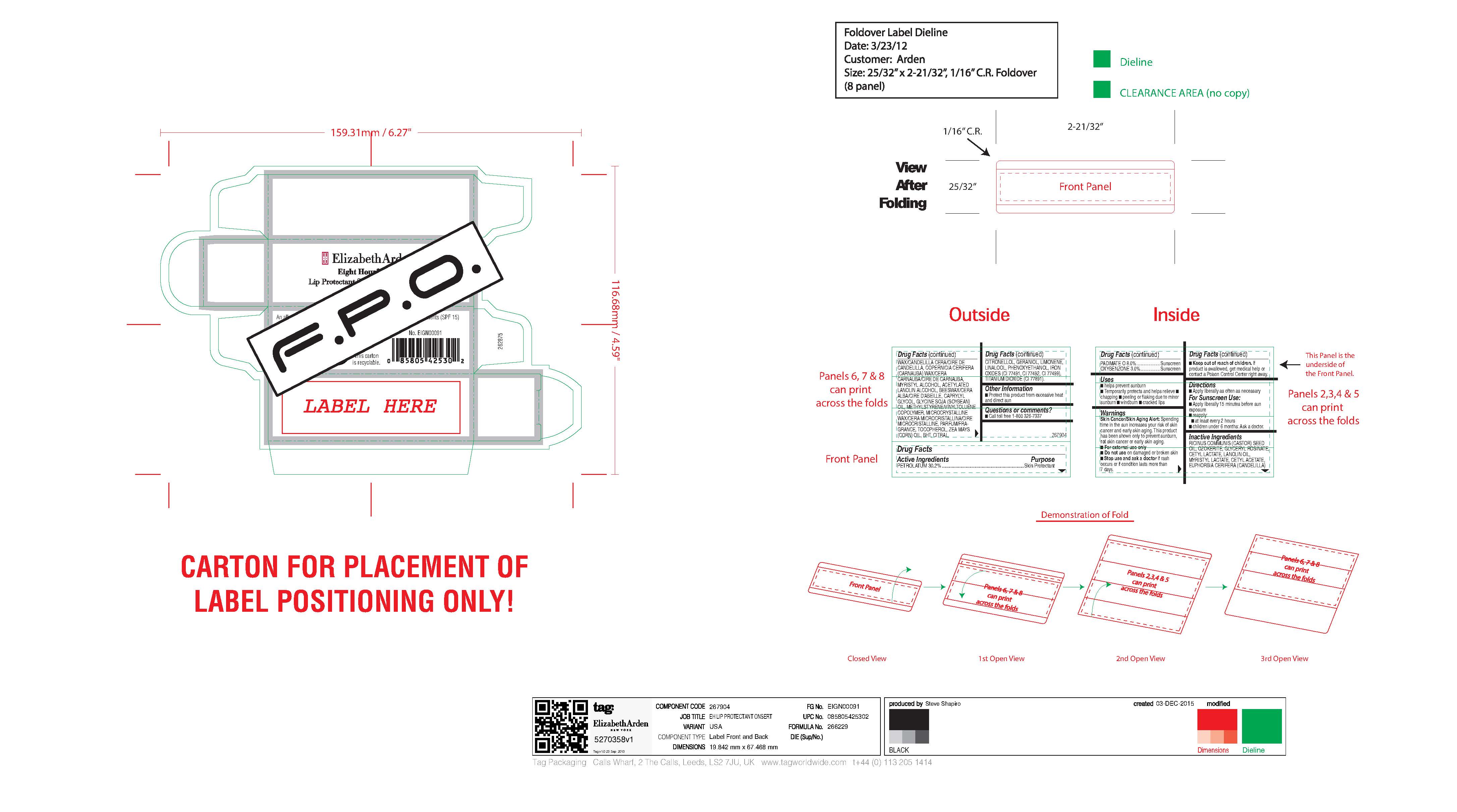 DRUG LABEL: EIGHT HOUR LIP PROTECTANT SPF 15
NDC: 10967-692 | Form: LIPSTICK
Manufacturer: REVLON
Category: otc | Type: HUMAN OTC DRUG LABEL
Date: 20241224

ACTIVE INGREDIENTS: AVOBENZONE 2 mg/1 g; OCTINOXATE 7.49475 mg/1 g; OXYBENZONE 3 mg/1 g; PETROLATUM 30.99938 mg/1 g
INACTIVE INGREDIENTS: BIS-DIGLYCERYL POLYACYLADIPATE-2; HYDROGENATED POLYISOBUTENE (1300 MW); BEESWAX; CERESIN; BHT; ACID YELLOW 23 ALUMINUM LAKE; LANOLIN; CETYL PEG/PPG-10/1 DIMETHICONE (HLB 2); ALPHA-TOCOPHEROL ACETATE; IRON OXIDES; BENZOIC ACID; SHEA BUTTER; COCONUT OIL; POLYETHYLENE; OCTYLDODECYL NEOPENTANOATE; MICA; HEXYL LAURATE; POLYBUTENE (1400 MW); DIISOSTEARYL MALATE; SYNTHETIC WAX (1200 MW); POLYGLYCERYL-4 ISOSTEARATE

ELIZABETH ARDEN EIGHT HOUR CREAM LIP PROTECTANT STICK SPF 15

Active Ingredients

Active Ingredients Purpose
PETROLATUM 30.2% ............. Skin Protectant
PADIMATE O 8.0%....................Sunscreen
OXYBENZONE 3.0%.................Sunscreen

Inactive Ingredients

RICINUS COMMUNIS (CASTOR) SEED OIL, OZOKERITE, GLYCERYL ROSINATE, CETYL LACTATE, LANOLIN OIL, MYRISTYL LACTATE, CETYL ACETATE, EUPHORBIA CERIFERA (CANDELILLA) WAX/CANDELILLA CERA/CIRE DE CANDELILLA, COPERNICIA CERIFERA (CARNAUBA) WAX/CERA CARNAUBA/CIRE DE CARNAUBA, MYRISTYL ALCOHOL, ACETYLATED LANOLIN ALCOHOL, BEESWAX/CERA ALBA/CIRE D'ABEILLE, CAPRYLYL GLYCOL, GLYCINE SOJA (SOYBEAN) OIL, METHYLSTYRENE/VINYLTOLUENE COPOLYMER, MICROCRYSTALLINE WAX/CERA MICROCRISTALLINA/CIRE MICROCRISTALLINE, PARFUM/FRAGRANCE, TOCOPHEROL, ZEA MAYS (CORN) OIL, BHT, CITRAL, CITRONELLOL, GERANIOL, LIMONENE, LINALOOL, PHENOXYETHANOL, IRON OXIDES (CI 77491, CI 77492, CI 77499), TITANIUM DIOXIDE (CI 77891).

Uses

- helps prevent sunburn
- Temporarily protects and helps relieve

- chapping

- peeling or flaking due to minor sunburn

- windburn

- cracked lips

Warnings

Skin Cancer/Skin Aging Alert: Spending time in the sun increases your risk of skin cancer and early skin aging. This product has been shown only to prevent sunburn, not skin cancer or early skin aging.

- For external use only
- Do not use on damaged or broken skin
- Stop use and ask a doctor if rash occurs or if condition lasts more than 7 days.
- Keep out of reach of children. If product is swallowed, get medical help or contact a Poison Control Center right away.

Directions for Use

Directions

- Apply liberally as often as necessary

For Sunscreen Use:

- Apply liberally 15 minutes before sun exposure
- reapply:

- at least every 2 hours

- children under 6 months: Ask a doctor.

DOSAGE AND ADMINISTRATION

As needed

INDICATIONS AND USAGE

- Helps prevent sunburn
- Temporarily protects and helps relieve
- chapping
- peeling or flaking due to minor sunburn
- windburn
- cracked lips

PURPOSE

Sunscreen

Skin Protectant

Keep out of reach of children. If product is swallowed, get medical help or contact a Poison Control Center right away.